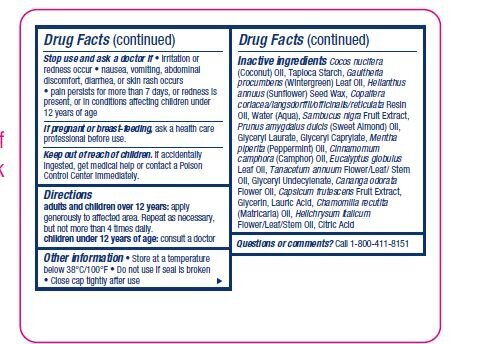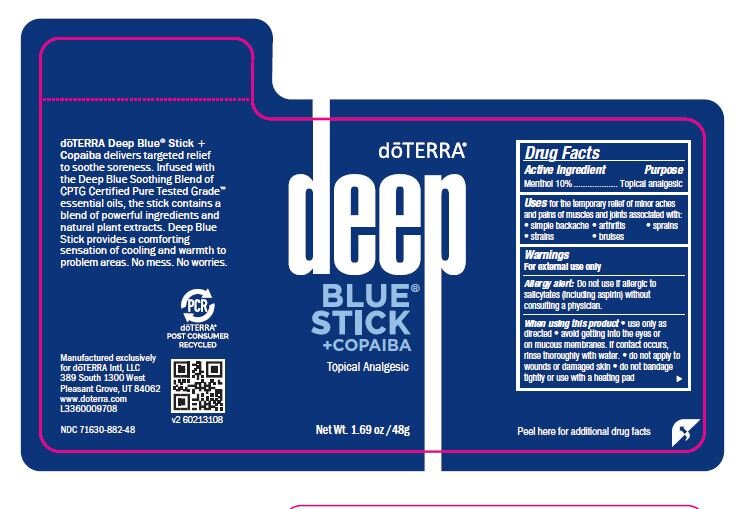 DRUG LABEL: Deep Blue
NDC: 71630-882 | Form: STICK
Manufacturer: dōTERRA International, LLC
Category: otc | Type: HUMAN OTC DRUG LABEL
Date: 20210715

ACTIVE INGREDIENTS: MENTHOL 10 g/100 g
INACTIVE INGREDIENTS: COCONUT OIL; STARCH, TAPIOCA; GAULTHERIA PROCUMBENS LEAF; HELIANTHUS ANNUUS SEED WAX; HELICHRYSUM ITALICUM FLOWER OIL; CITRIC ACID MONOHYDRATE; ALMOND OIL; PEPPERMINT OIL; CAMPHOR OIL; EUCALYPTUS OIL; MATRICARIA CHAMOMILLA FLOWERING TOP OIL; GLYCERIN; CANANGA OIL; SAMBUCUS NIGRA SUBSP. CERULEA FRUIT; GLYCERYL LAURATE; GLYCERYL CAPRYLATE; TANACETUM ANNUUM FLOWERING TOP OIL; GLYCERYL 1-UNDECYLENATE; TABASCO PEPPER; LAURIC ACID; WATER; COPAIBA OIL

Deep Blue Stick with Copaiba 300904-A

Active Ingredient

Menthol 10%

PURPOSE

Topical analgesic

INDICATIONS AND USAGE

Uses for the temporary relief of minor aches
and pains of muscles and joints associated with:
• simple backache • arthritis • sprains
• strains • bruises

WARNINGS

For external use only
Allergy alert: Do not use if allergic to
salicylates (including aspirin) without
consulting a physician.

When using this product • use only as
directed • avoid getting into the eyes or
on mucous membranes. If contact occurs,
rinse thoroughly with water. • do not apply to
wounds or damaged skin • do not bandage
tightly or use with a heating pad

PREGNANCY OR BREAST FEEDING

If pregnant or breast-feeding, ask a health care
professional before use.

Keep out of reach of children. If accidentally
ingested, get medical help or contact a Poison
Control Center immediately.

Stop use and ask a doctor if • irritation or
redness occur • nausea, vomiting, abdominal
discomfort, diarrhea, or skin rash occurs
• pain persists for more than 7 days, or redness is
present, or in conditions affecting children under
12 years of age

Directions
adults and children over 12 years: apply
generously to affected area. Repeat as necessary,
but not more than 4 times daily.
children under 12 years of age: consult a doctor

Other information • Store at a temperature
below 38°C/100°F • Do not use if seal is broken
• Close cap tightly after use

Inactive ingredients Cocos nucifera
(Coconut) Oil, Tapioca Starch, Gaultheria
procumbens (Wintergreen) Leaf Oil, Helianthus
annuus (Sunflower) Seed Wax, Copaifera
coriacea/langsdorffii/officinalis/reticulata Resin
Oil, Water (Aqua), Sambucus nigra Fruit Extract,
Prunus amygdalus dulcis (Sweet Almond) Oil,
Glyceryl Laurate, Glyceryl Caprylate, Mentha
piperita (Peppermint) Oil, Cinnamomum
camphora (Camphor) Oil, Eucalyptus globulus
Leaf Oil, Tanacetum annuum Flower/Leaf/ Stem
Oil, Glyceryl Undecylenate, Cananga odorata
Flower Oil, Capsicum frutescens Fruit Extract,
Glycerin, Lauric Acid, Chamomilla recutita
(Matricaria) Oil, Helichrysum italicum
Flower/Leaf/Stem Oil, Citric Acid

Questions or comments? Call 1-800-411-8151

Active Ingredient Purpose
Menthol 10%................... Topical analgesic

PACKAGE LABEL

doTERRA Deep Blue Stick +Copaiba

Topical analgesic

Net Wt. 1.69 oz/48g